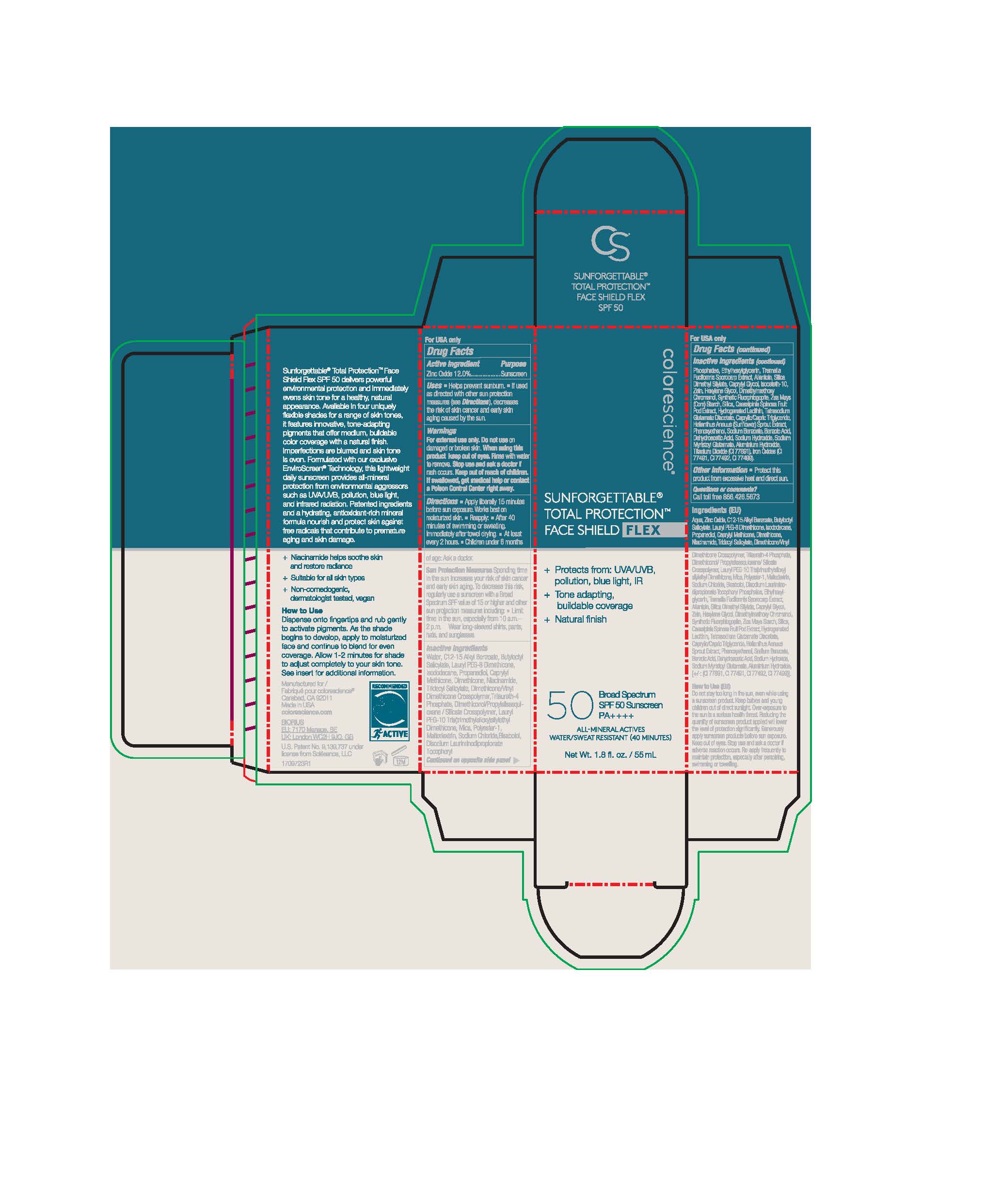 DRUG LABEL: Sunforgettable Total Protection Face Shield Flex
NDC: 68078-042 | Form: LOTION
Manufacturer: Colorescience
Category: otc | Type: HUMAN OTC DRUG LABEL
Date: 20251015

ACTIVE INGREDIENTS: ZINC OXIDE 135.6 mg/1 mL
INACTIVE INGREDIENTS: SODIUM MYRISTOYL GLUTAMATE; TRIDECYL SALICYLATE; DIMETHYLMETHOXY CHROMANOL; TITANIUM DIOXIDE; CAPRYLYL GLYCOL; MYRISTYL TRISILOXANE; LAURYL PEG-9 POLYDIMETHYLSILOXYETHYL DIMETHICONE; ALLANTOIN; .ALPHA.-BISABOLOL, (+)-; SILICON DIOXIDE; DIMETHICONE/VINYL DIMETHICONE CROSSPOLYMER (SOFT PARTICLE); TRILAURETH-4 PHOSPHATE; BUTYLOCTYL SALICYLATE; ISODODECANE; NIACINAMIDE; WATER; DIMETHICONOL/PROPYLSILSESQUIOXANE/SILICATE CROSSPOLYMER (450000000 MW); ETHYLHEXYLGLYCERIN; HEXYLENE GLYCOL; DEHYDROACETIC ACID; PROPANEDIOL; TETRASODIUM GLUTAMATE DIACETATE; SODIUM CHLORIDE; PHENOXYETHANOL; TREMELLA FUCIFORMIS FRUITING BODY; MALTODEXTRIN; DIMETHICONE; ALKYL (C12-15) BENZOATE; DISODIUM LAURIMINODIPROPIONATE TOCOPHERYL PHOSPHATES; ISOCETETH-10; CAESALPINIA SPINOSA FRUIT POD; HELIANTHUS ANNUUS SPROUT; MICA; SILICA DIMETHYL SILYLATE; ZEIN; ALUMINUM HYDROXIDE

Sunforgettable Total Protection Face Shield Flex